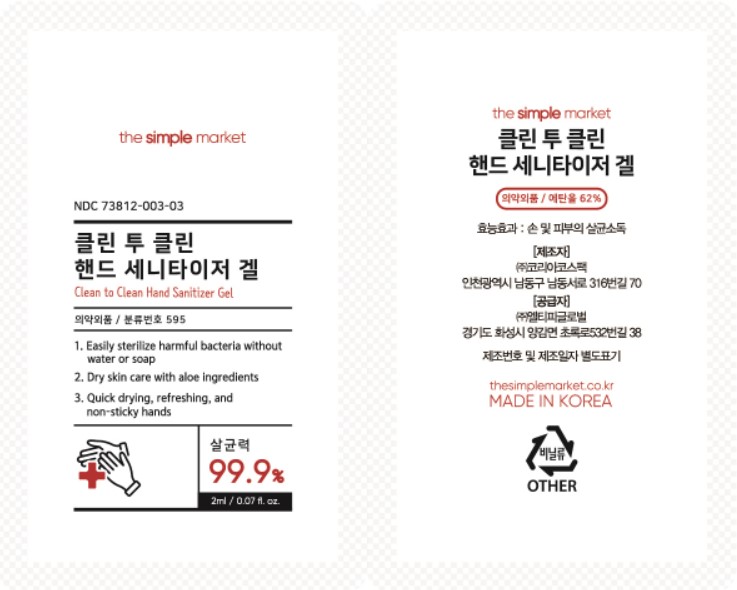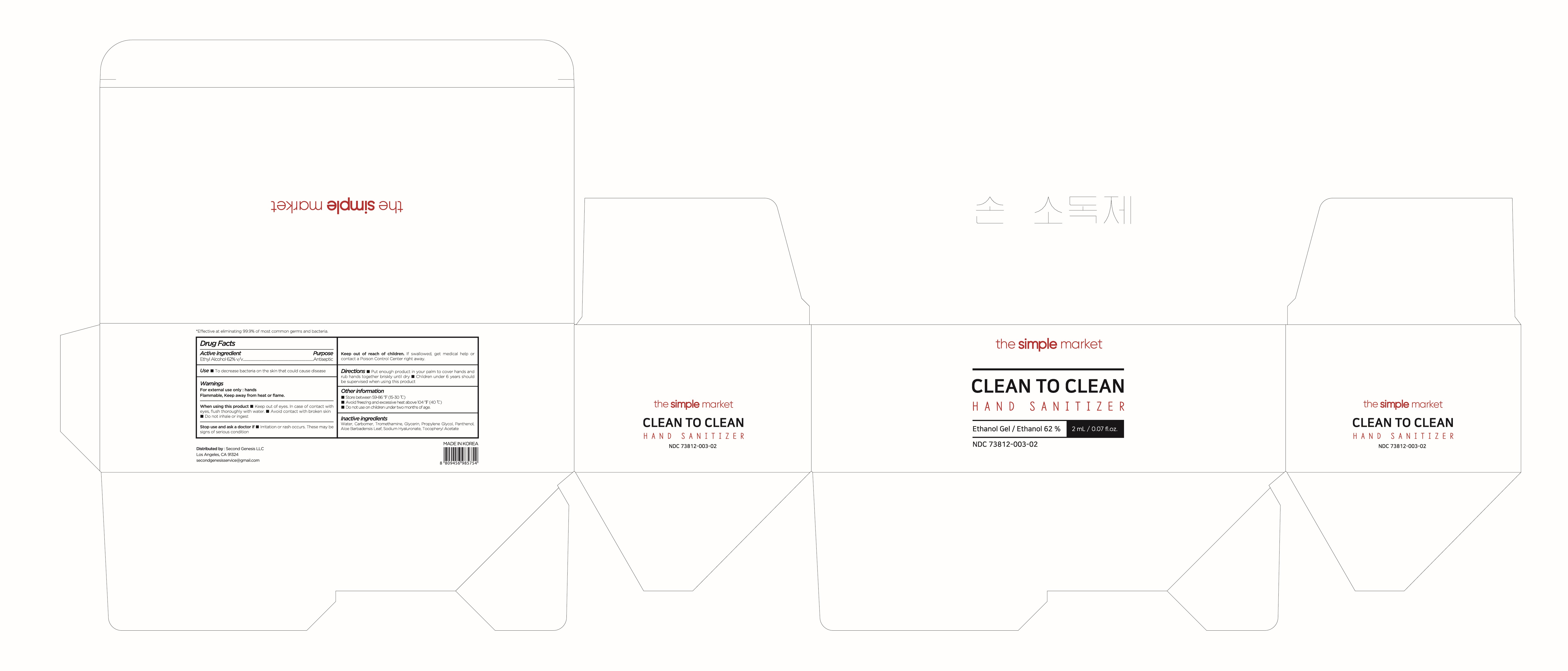 DRUG LABEL: CLEAN TO CLEAN HAND SANITIZER
NDC: 73812-003 | Form: GEL
Manufacturer: LTP Global
Category: otc | Type: HUMAN OTC DRUG LABEL
Date: 20200529

ACTIVE INGREDIENTS: ALCOHOL 62 mL/100 mL
INACTIVE INGREDIENTS: HYALURONATE SODIUM; ALPHA-TOCOPHEROL ACETATE; ALOE VERA LEAF; TROMETHAMINE; PROPYLENE GLYCOL; GLYCERIN; CARBOMER HOMOPOLYMER TYPE B (ALLYL PENTAERYTHRITOL CROSSLINKED); WATER; PANTHENOL

Active Ingredient(s)

Ethyl Alcohol 62% v/v

Purpose

Antiseptic

Use

- to decrease bacteria on the skin that could cause disease

Warnings

For external use only : hands

Flammable. Keep away from heat or flame.

- When using this product keep out of eyes. In case of contact with eyes, flush thoroughly with water.
- avoid contact with broken skin
- do not inhale or ingest

Stop use and ask a doctor if

- irritation and rash occurs. These may be signs of serious condition

Keep out of reach of children. If swallowed, get medical help or contact a Poison Control Center right away.

Directions

- Put enough product in your palm to cover hands and rub hands together briskly until dry
- Children under 6 years should be supervised when using this product

Other information

- Store between 15-30C (59-86F)
- Avoid freezing and excessive heat above 40C (104F)
- Do not use on children under two months of age.

Inactive ingredients

Water, Carbomer, Tromethamin, Glycerin, Propylene Glycol, Panthenol, Aloe Barbadensis Leaf, Sodium Hyalunate, Tocopheryl Acetate